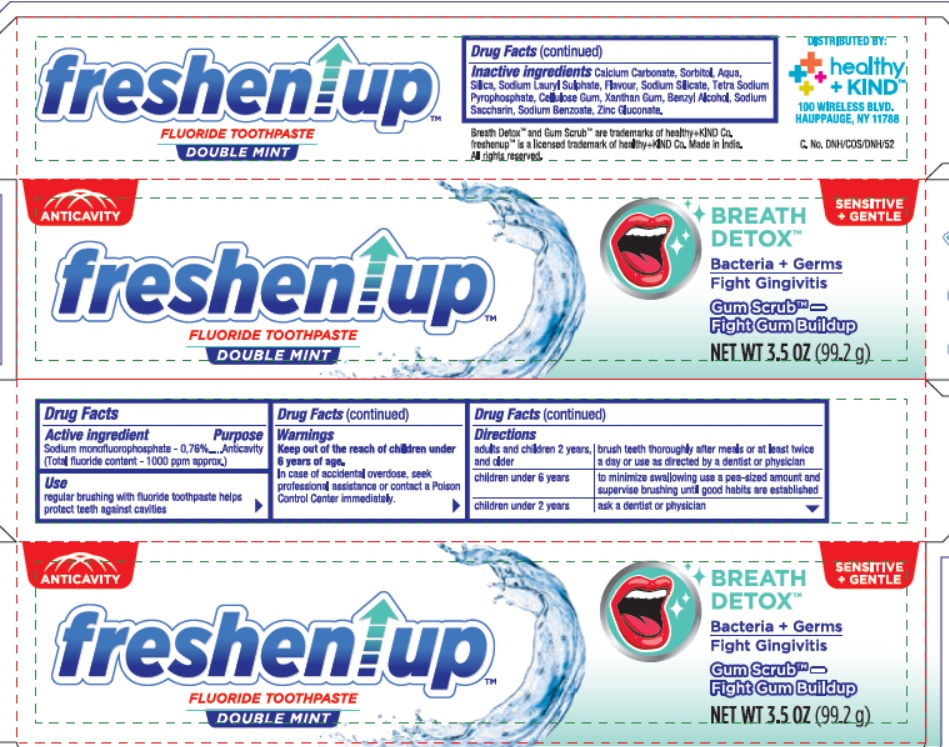 DRUG LABEL: Freshenup Fluoride Double Mint
NDC: 52553-049 | Form: PASTE, DENTIFRICE
Manufacturer: U. S. Nonwovens Corp
Category: otc | Type: HUMAN OTC DRUG LABEL
Date: 20190814

ACTIVE INGREDIENTS: Sodium Monofluorophosphate 7.6 mg/1 g
INACTIVE INGREDIENTS: CALCIUM CARBONATE; SORBITOL; WATER; SILICON DIOXIDE; SODIUM LAURYL SULFATE; SODIUM SILICATE; SODIUM PYROPHOSPHATE; CARBOXYMETHYLCELLULOSE SODIUM, UNSPECIFIED FORM; XANTHAN GUM; BENZYL ALCOHOL; SACCHARIN SODIUM; SODIUM BENZOATE; ZINC GLUCONATE

Freshenup Fluoride Toothpaste

Drug Facts

Active ingredient

Sodium monofluorophosphate 0.76% (Total Fluoride Content - 1000 ppm approx)

Purpose

Anticavity

Use

regular brushing with fluoride toothpaste helps protect teeth against cavities

Warnings

Keep out of the reach of children under 6 years of age. In case of accidental overdose, seek professional assistance or contact a Poison Control Center right away.

Directions

adults and children 2 years and older | brush teeth thoroughly after meals or at least twice a day or use as directed by a dentist or physician
children under 6 years | to minimize swallowing use a pea sized amount and supervise brushing until good habits are established
children under 2 years | ask a dentist or physician

Inactive ingredients

Calcium Carbonate, Sorbitol, Aqua, Silica, Sodium Lauryl Sulphate, Flavour, Sodium Silicate, Tetra Sodium Pyrophosphate, Cellulose Gum, Xanthan Gum, Benzyl Alcohol, Sodium Saccharin, Sodium Benzoate, Zinc Gluconate

Breath DetoxTM and Gum ScrubTM are trademarks of healthy + KIND Co.

freshenup is a licensed trademark of healthy+KIND Co. Made In India. All rights reserved

PRINCIPAL DISPLAY PANEL

NDC 52553-049-02

ANTICAVITY

Freshenup

FLUORIDE TOOTHPASTE

DOUBLE MINT

SENSITIVE + GENTLE

BREATH DETOX

Bacteria + Germs

Fight Gengivitis

Gum ScrubTM - Fight Gum Building

NET WT 3.5 OZ (99.2 g)